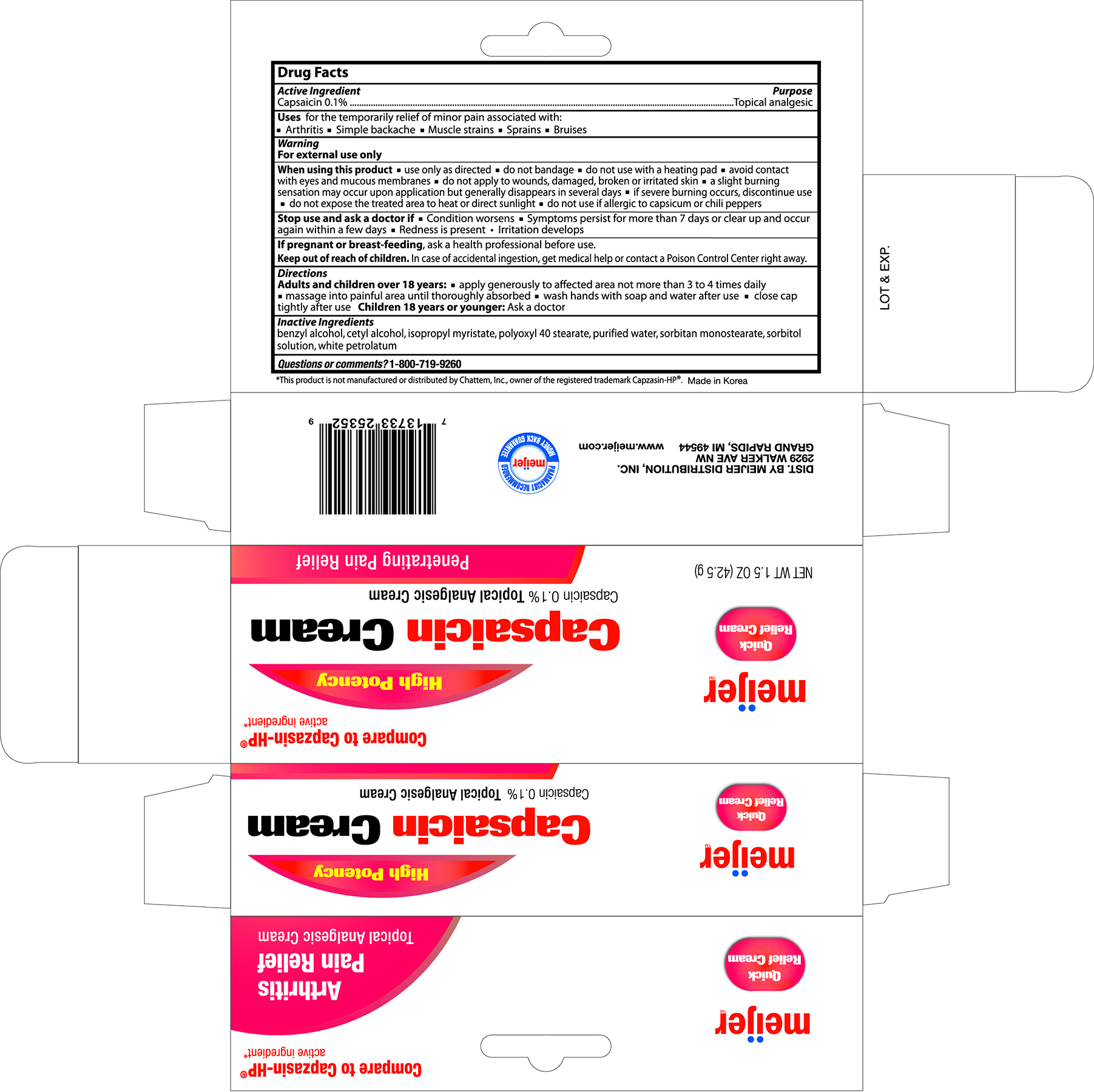 DRUG LABEL: MEIJER CAPSAICIN
NDC: 41250-256 | Form: CREAM
Manufacturer: MEIJER, INC.
Category: otc | Type: HUMAN OTC DRUG LABEL
Date: 20161011

ACTIVE INGREDIENTS: CAPSAICIN 0.1 g/10 g
INACTIVE INGREDIENTS: BENZYL ALCOHOL; CETYL ALCOHOL; ISOPROPYL MYRISTATE; POLYOXYL 40 STEARATE; WATER; SORBITAN MONOSTEARATE; SORBITOL; PETROLATUM

Active ingredient Purpose

Capsaicin 0.1%........................................................................Topical analgesic

Uses

For the temporary relief of minor pain associated with:

- Arthritis
- Simple backache
- Muscle strains
- Sprains
- Bruises

Warnings

For external use only

When using this product

- use only as directed
- do not bandage
- do not use with heating pad
- avoid contact with eyes and mucous membranes
- do not apply to wounds, damaged, broken or irritated skin
- a slight burning sensation may occur upon application but generally disappears in several days
- if severe burning occurs, discontinue use
- do not expose the treated area to heat or direct sunlight
- do not use if allergic to capsicum or chili peppers

Stop use and ask a doctor if

- condition worsens
- symptoms persist for more than 7 days or clear up and occur again within a few days
- redness is present
- irritation develops

PREGNANCY OR BREAST FEEDING

If pregnant or breast-feeding, ask a health professional before use.

Keep out of reach of children.

In case of accidental ingestion, get medical help or contact a Poison Control Center right away.

Directions

Adults and children over 18 years:

- apply generously to affected area not more than 3 to 4 times daily
- massage into painful area until thoroughly absorbed
- wash hands with soap and water after use
- close cap tightly after use

Children 18 years or younger: Ask a doctor

Inactive ingredients

Benzyl alcohol, cetyl alcohol, isopropyl myristate, polyoxyl 40 stearate, purified water, sorbitan, monostearate, sorbitol solution, white petrolatum

DOSAGE AND ADMINISTRATION

DIST. BY MEIJER DISTRIBUTION, INC.

2929 WALKER AVE NW

GRAND RAPIDS, MI 49544

www.meijer.com

Made in Korea